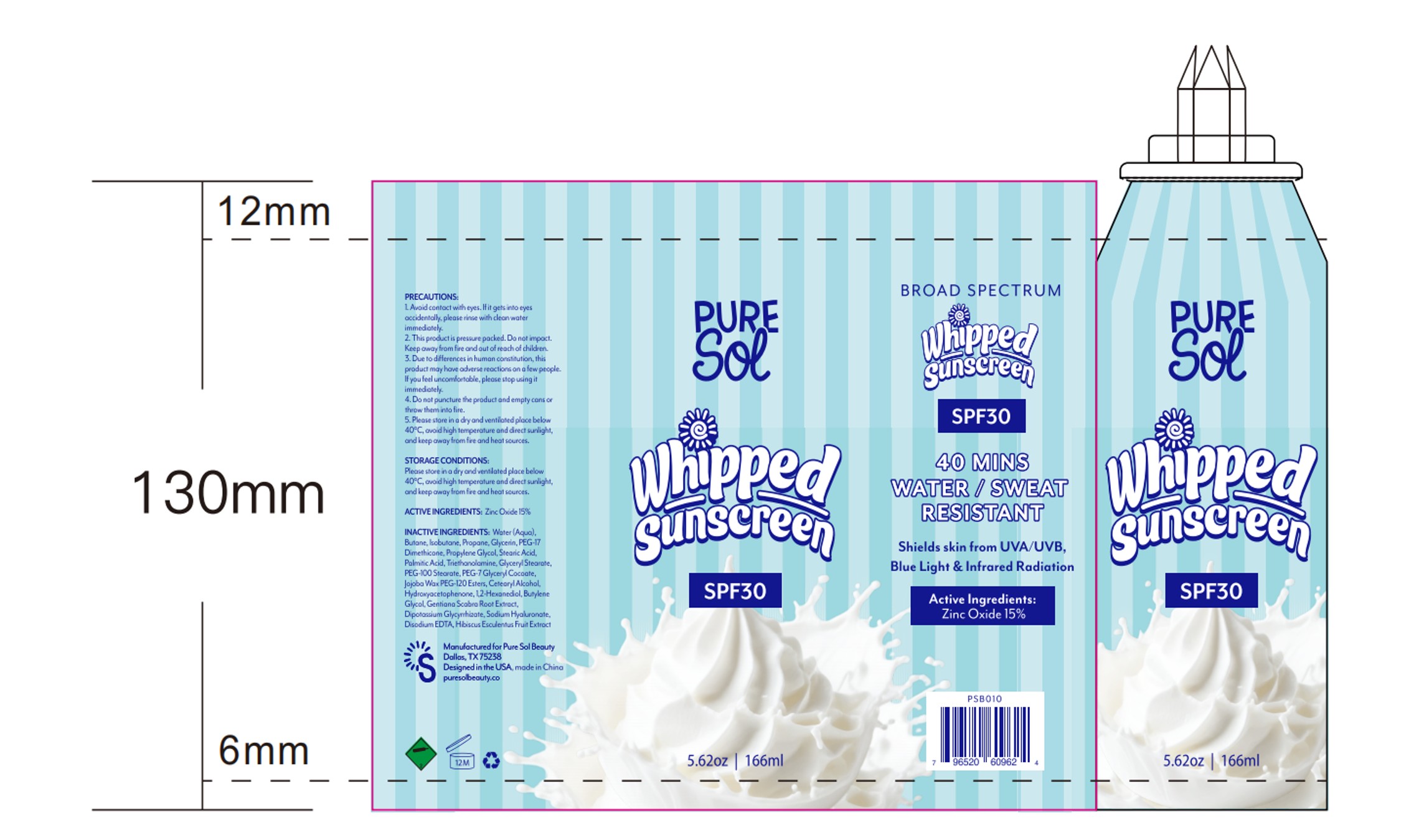 DRUG LABEL: spf30 mineral sunscreen mousse
NDC: 82723-031 | Form: SPRAY
Manufacturer: Aopline Health Industry Technology (Guangzhou) Co., Ltd.
Category: otc | Type: HUMAN OTC DRUG LABEL
Date: 20250827

ACTIVE INGREDIENTS: ZINC OXIDE 15 g/100 mL
INACTIVE INGREDIENTS: WATER; BUTANE; PROPANE; GLYCERIN; DIPOTASSIUM GLYCYRRHIZATE; 1,2-HEXANEDIOL; PALMITIC ACID; PEG-12 DIMETHICONE; PROPYLENE GLYCOL; PEG-100 STEARATE; HYDROXYACETOPHENONE; SODIUM HYALURONATE; EDETATE DISODIUM; ISOBUTANE; STEARIC ACID; TROLAMINE; GLYCERYL STEARATE; PEG-7 GLYCERYL COCOATE; HYDROGENATED JOJOBA OIL/JOJOBA OIL, RANDOMIZED (IODINE VALUE 64-70); CETEARYL ALCOHOL; BUTYLENE GLYCOL; GENTIANA SCABRA ROOT; OKRA

ACTIVE INGREDIENT

Zinc Oxide（nano）15%

INACTIVE INGREDIENT

Water
Butane
Isobutane
Propane
Glycerin
PEG-17 Dimethicone
Propylene Glycol
Stearic Acid
Palmitic Acid
Triethanolamine
Glyceryl Stearate
PEG-100 Stearate
PEG-7 Glyceryl Cocoate
Jojoba Wax PEG-120 Esters
Cetearyl Alcohol
Hydroxyacetophenone
1,2-Hexanediol
Butylene Glycol
Gentiana Scabra Root Extract
Dipotassium Glycyrrhizate
Sodium Hyaluronate
Disodium EDTA
Hibiscus Esculentus Fruit Extract

PURPOSE

Helps prevent sunbum, if used as directed withother sun protection measures (see Direciions), decreasesthe risk of skin cancer and eary aging caused by the sun

WARNINGS

For extemal use onl,.
Do not use on damaged or broken skn,
When using this product keep out of cyes, Rinse withwater to remowe,
Siop use and ask a doctor if rash cccurs.Keep out of reach of children, lf product is swalkawed, getmedical help or contact a Potson Conirol Centre right away.Wlay stain some fabrics.

Stop use and ask a doctor if rash occurs

Do not use on damaged or broken skin

WHEN USING

Apply liberaly 15 minues before sunexposure,

Reapply: After 80 minutes of swimming orsseating,

lmmedabely after touel drying.. At leastevery 2 hours,

keep out of children to use it

INDICATIONS AND USAGE

1.Avoid contact with eyes. lf it gets into eye accidentally, please rinse with clean water 2. This product is pressure pocked. Do not impact. Keep away from fire out of reach of children.3. Due to differences in human constitution, this product may have adheres reactions an a few people you feel uncontactable, please stop using
4. Do not puncture the product and empty cans or show then into fire.5. Please store in a dry and place below40℃, avoid high temperature and direct sunlight,、

DOSAGE AND ADMINISTRATION

Directions: Apply liberaly 15 minues before sunexposure, e Reapply: After 80 minutes of swimming or seating,. lmmedabely after touel drying.. At leastevery 2 hours,